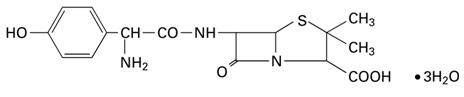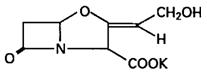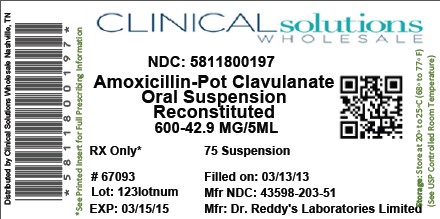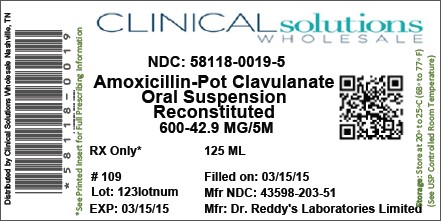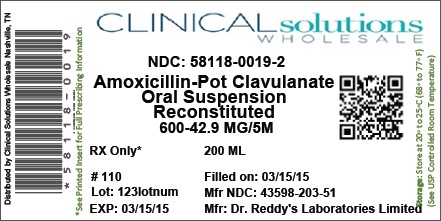 DRUG LABEL: Amoxicillin and Clavulanate Potassium
NDC: 58118-0019 | Form: POWDER, FOR SUSPENSION
Manufacturer: Clinical Solutions Wholesale
Category: prescription | Type: HUMAN PRESCRIPTION DRUG LABEL
Date: 20160808

ACTIVE INGREDIENTS: AMOXICILLIN 600 mg/5 mL; CLAVULANATE POTASSIUM 42.9 mg/5 mL
INACTIVE INGREDIENTS: SILICON DIOXIDE; XANTHAN GUM; ASPARTAME; CARBOXYMETHYLCELLULOSE SODIUM, UNSPECIFIED FORM

Amoxicillin and Clavulanate Potassium 600 mg/42.9 mg per 5 mL
Powder for Oral Suspension

1111
PRESCRIBING INFORMATION

To reduce the development of drug-resistant bacteria and maintain the effectiveness of Amoxicillin and Clavulanate Potassium 600 mg/42.9 mg per 5 mL and other antibacterial drugs, Amoxicillin and Clavulanate Potassium 600 mg/42.9 mg per 5 mL should be used only to treat or prevent infections that are proven or strongly suspected to be caused by bacteria.

DESCRIPTION

Amoxicillin and Clavulanate Potassium 600 mg/42.9 mg per 5 mL is an oral antibacterial combination consisting of the semisynthetic antibiotic amoxicillin and the β-lactamase inhibitor, clavulanate potassium (the potassium salt of clavulanic acid). Amoxicillin is an analog of ampicillin, derived from the basic penicillin nucleus, 6-aminopenicillanic acid. The amoxicillin molecular formula is C16H19N3O5S•3H2O, and the molecular weight is 419.46. Chemically, amoxicillin is (2 S,5 R,6 R)-6-[(R)-(-)-2-Amino-2-(p-hydroxyphenyl)acetamido]-3,3-dimethyl-7-oxo-4-thia-1-azabicyclo[3.2.0]heptane-2-carboxylic acid trihydrate and may be represented structurally as:

Clavulanic acid is produced by the fermentation of Streptomyces clavuligerus. It is a β-lactam structurally related to the penicillins and possesses the ability to inactivate a wide variety of β-lactamases by blocking the active sites of these enzymes. Clavulanic acid is particularly active against the clinically important plasmid-mediated β-lactamases frequently responsible for transferred drug resistance to penicillins and cephalosporins. The clavulanate potassium molecular formula is C8H8KNO5, and the molecular weight is 237.25. Chemically, clavulanate potassium is potassium (Z)-(2 R ,5 R)-3-(2-hydroxyethylidene)-7-oxo-4-oxa-1-azabicyclo[3.2.0]-heptane-2-carboxylate and may be represented structurally as:

Inactive Ingredients:

Powder for Oral Suspension- Colloidal silicon dioxide, strawberry cream flavor, xanthan gum, aspartamea, sodium carboxymethylcellulose, and silicon dioxide.

a See PRECAUTIONS— Information for the Patient/ Phenylketonurics.

Each 5 mL of reconstituted 600 mg/42.9 mg per 5 mL oral suspension of Amoxicillin and Clavulanate Potassium contains 0.23 mEq potassium.

CLINICAL PHARMACOLOGY

The pharmacokinetics of amoxicillin and clavulanate were determined in a study of 19 pediatric patients, 8 months to 11 years, given Amoxicillin and Clavulanate Potassium 600 mg/42.9 mg per 5 mL at an amoxicillin dose of 45 mg/kg q12h with a snack or meal. The mean plasma amoxicillin and clavulanate pharmacokinetic parameter values are listed in the following table.

Table 1. Mean (±SD) Plasma Amoxicillin and Clavulanate Pharmacokinetic Parameter Values Following Administration of 45 mg/kg of Amoxicillin and Clavulanate Potassium 600 mg/42.9 mg per 5 mL Every 12 Hours to Pediatric Patients
PARAMETER [Arithmetic mean ± standard deviation, except T max values which are medians (ranges).] | AMOXICILLIN | CLAVULANATE
Cmax (mcg/mL) | 15.7 ± 7.7 | 1.7 ± 0.9
Tmax (hr) | 2.0 (1.0 - 4.0) | 1.1 (1.0 - 4.0)
AUC0-t (mcg⋅hr/mL) | 59.8 ± 20.0 | 4.0 ± 1.9
T1/2 (hr) | 1.4 ± 0.3 | 1.1 ± 0.3
CL/F (L/hr/kg) | 0.9 ± 0.4 | 1.1 ± 1.1

The effect of food on the oral absorption of Amoxicillin and Clavulanate Potassium 600 mg/42.9 mg per 5 mL has not been studied.

Approximately 50% to 70% of the amoxicillin and approximately 25% to 40% of the clavulanic acid are excreted unchanged in urine during the first 6 hours after administration of 10 mL of 250 mg/5 mL suspension of amoxicillin and clavulanate potassium.

Concurrent administration of probenecid delays amoxicillin excretion but does not delay renal excretion of clavulanic acid.

Neither component in Amoxicillin and Clavulanate Potassium 600 mg/42.9 mg per 5 mL is highly protein-bound; clavulanic acid has been found to be approximately 25% bound to human serum and amoxicillin approximately 18% bound.

Oral administration of a single dose of Amoxicillin and Clavulanate Potassium 600 mg/42.9 mg per 5 mL at 45 mg/kg (based on the amoxicillin component) to pediatric patients, 9 months to 8 years, yielded the following pharmacokinetic data for amoxicillin in plasma and middle ear fluid (MEF).

Table 2. Amoxicillin Concentrations in Plasma and Middle Ear Fluid Following Administration of 45 mg/kg of Amoxicillin and Clavulanate Potassium 600 mg/42.9 mg per 5 mL to Pediatric Patients
Timepoint |  | Amoxicillin concentration in plasma (mcg/mL) | Amoxicillin concentration in MEF (mcg/mL)
1 hour | mean median range | 7.7 9.3 1.5 - 14.0 (n = 5) | 3.2 3.5 0.2 - 5.5 (n = 4)
2 hour | mean median range | 15.7 13.0 11.0 - 25.0 (n= 7) | 3.3 2.4 1.9 - 6 (n = 5)
3 hour | mean median range | 13.0 12.0 5.5 - 21.0 (n = 5) | 5.8 6.5 3.9 - 7.4 (n = 5)

Dose administered immediately prior to eating.

Amoxicillin diffuses readily into most body tissues and fluids with the exception of the brain and spinal fluid. The results of experiments involving the administration of clavulanic acid to animals suggest that this compound, like amoxicillin, is well distributed in body tissues.

Microbiology:

Amoxicillin is a semisynthetic antibiotic with a broad spectrum of bactericidal activity against many gram-positive and gram-negative microorganisms. Amoxicillin is, however, susceptible to degradation by β-lactamases, and therefore, its spectrum of activity does not include organisms which produce these enzymes. Clavulanic acid is a β-lactam, structurally related to penicillin, which possesses the ability to inactivate a wide range of β-lactamase enzymes commonly found in microorganisms resistant to penicillins and cephalosporins. In particular, it has good activity against the clinically important plasmid-mediated β-lactamases frequently found responsible for transferred drug resistance.

The clavulanic acid component of Amoxicillin and Clavulanate Potassium 600 mg/42.9 mg per 5 mL protects amoxicillin from degradation by β-lactamase enzymes and effectively extends the antibiotic spectrum of amoxicillin to include many bacteria normally resistant to amoxicillin and other β-lactam antibiotics. Thus, Amoxicillin and Clavulanate Potassium 600 mg/42.9 mg per 5 mL possesses the distinctive properties of a broad-spectrum antibiotic and a β-lactamase inhibitor.

Amoxicillin/clavulanic acid has been shown to be active against most isolates of the following microorganisms, both in vitro and in clinical infections as described in the INDICATIONS AND USAGE section.

Aerobic Gram-Positive Microorganisms:

Streptococcus pneumoniae (including isolates with penicillin MICs ≤ 2 mcg/mL)

Aerobic Gram-Negative Microorganisms:

Haemophilus influenzae (including β-lactamase–producing isolates)

Moraxella catarrhalis (including β-lactamase–producing isolates)

The following in vitro data are available, but their clinical significance is unknown.

At least 90% of the following microorganisms exhibit in vitro minimum inhibitory concentrations (MICs) less than or equal to the susceptible breakpoint for amoxicillin/clavulanic acid. However, the safety and efficacy of amoxicillin/clavulanic acid in treating infections due to these microorganisms have not been established in adequate and well-controlled trials.

Aerobic Gram-Positive Microorganisms:

Staphylococcus aureus (including β-lactamase–producing isolates)

NOTE: Staphylococci which are resistant to methicillin/oxacillin must be considered resistant to amoxicillin/clavulanic acid.

Streptococcus pyogenes

NOTE: S. pyogenes do not produce β-lactamase, and therefore, are susceptible to amoxicillin alone. Adequate and well-controlled clinical trials have established the effectiveness of amoxicillin alone in treating certain clinical infections due to S. pyogenes.

Susceptibility Test Methods:

When available, the clinical microbiology laboratory should provide cumulative results of in vitro susceptibility test results for antimicrobial drugs used in local hospitals and practice areas to the physician as periodic reports that describe the susceptibility profile of nosocomial and community-acquired pathogens. These reports should aid the physician in selecting the most effective antimicrobial.

Dilution Technique:

Quantitative methods are used to determine antimicrobial minimum inhibitory concentrations (MICs). These MICs provide estimates of the susceptibility of bacteria to antimicrobial compounds. The MICs should be determined using a standardized procedure.^1,2 Standardized procedures are based on dilution methods (broth for S. pneumoniae and H. influenzae) or equivalent with standardized inoculum concentration and standardized concentrations of amoxicillin/clavulanate potassium powder.

The recommended dilution pattern utilizes a constant amoxicillin/clavulanate potassium ratio of 2 to 1 in all tubes with varying amounts of amoxicillin. MICs are expressed in terms of the amoxicillin concentration in the presence of clavulanic acid at a constant 2 parts amoxicillin to 1 part clavulanic acid. The MIC values should be interpreted according to criteria provided in Table 3.

Diffusion Technique:

Quantitative methods that require measurement of zone diameters also provides reproducible estimates of the susceptibility of bacteria to antimicrobials. One such standardized technique requires the use of a standardized inoculum concentration.^2,3 This procedure uses paper disks impregnated with 30 mcg amoxicillin/clavulanate potassium (20 mcg amoxicillin plus 10 mcg clavulanate potassium) to test susceptibility of microorganisms to amoxicillin/clavulanate potassium. Disk diffusion zone sizes should be interpreted according to criteria provided in Table 3.

Table 3. Susceptibility Test Result Interpretive Criteria for Amoxicillin/Clavulanate Potassium
Pathogen | Minimum Inhibitory Concentration (mcg/mL) |  |  | Disk Diffusion (Zone Diameter in mm)
Pathogen | S | I | R | S | I | R
Streptococcus pneumoniae (non-meningitis isolates) | ≤ 2/1 | 4/2 | ≥ 8/4 | Not Applicable (NA)
Haemophilus influenzae | ≤ 4/2 | NA | ≥ 8/4 | ≥ 20 | NA | ≤ 19

NOTE: Susceptibility of S. pneumoniae should be determined using a 1-mcg oxacillin disk. Isolates with oxacillin zone sizes of ≥ 20 mm are susceptible to amoxicillin/clavulanic acid. An amoxicillin/clavulanic acid MIC should be determined on isolates of S. pneumoniae with oxacillin zone sizes of ≤ 19 mm.

NOTE: β-lactamase–negative, ampicillin-resistant H. influenzae isolates must be considered resistant to amoxicillin/clavulanic acid.

A report of S (“Susceptible”) indicates that the antimicrobial is likely to inhibit growth of the pathogen if the antimicrobial compound in the blood reaches the concentration usually achievable. A report of I (“Intermediate”) indicates that the result should be considered equivocal, and, if the microorganism is not fully susceptible to alternative, clinically feasible antimicrobials, the test should be repeated. This category implies possible clinical applicability in body sites where the drug is physiologically concentrated or in situations where high doses of antimicrobial can be used. This category also provides a buffer zone that prevents small uncontrolled technical factors from causing major discrepancies in interpretation. A report of R (“Resistant”) indicates that the antimicrobial is not likely to inhibit growth of the pathogen if the antimicrobial compound in the blood reaches the concentration usually achievable; other therapy should be selected.

Standardized susceptibility test procedures require the use of quality control microorganisms to determine the performance of the test procedures.^1-3 Standard amoxicillin/clavulanate potassium powder should provide the MIC ranges for the quality control organisms in Table 4. For the disk diffusion technique, the 30 mcg-amoxicillin/clavulanate potassium disk should provide the zone diameter ranges for the quality control organisms in Table 4.

Table 4. Acceptable Quality Control Ranges for Amoxicillin/Clavulanate Potassium
Quality Control Organism | Minimum Inhibitory Concentration Range (mcg/mL) | Disk Diffusion (Zone Diameter Range in mm)
Escherichia coli ATCC® [ATCC is a trademark of the American Type Culture Collection.] 35218 [When using Haemophilus Test Medium (HTM).] (H. influenzae quality control) | 4/2 to 16/8 | 17 to 22
Haemophilus influenzae ATCC 49247 | 2/1 to 16/8 | 15 to 23
Streptococcus pneumoniae ATCC 49619 | 0.03/0.016 to 0.12/0.06 | NA

INDICATIONS AND USAGE

Amoxicillin and Clavulanate Potassium 600 mg/42.9 mg per 5 mL is indicated for the treatment of pediatric patients with recurrent or persistent acute otitis media due to S. pneumoniae (penicillin MICs ≤ 2 mcg/mL), H. influenzae (including β-lactamase–producing strains), or
M. catarrhalis (including β-lactamase–producing strains) characterized by the following risk factors:

- antibiotic exposure for acute otitis media within the preceding 3 months, and either of the following:
  - age ≤ 2 years
  - daycare attendance

[See CLINICAL PHARMACOLOGY, Microbiology.]

NOTE: Acute otitis media due to S. pneumoniae alone can be treated with amoxicillin. Amoxicillin and Clavulanate Potassium 600 mg/42.9 mg per 5 mL is not indicated for the treatment of acute otitis media due to S. pneumoniae with penicillin MIC ≥ 4 mcg/mL.

Therapy may be instituted prior to obtaining the results from bacteriological studies when there is reason to believe the infection may involve both S. pneumoniae (penicillin MIC ≤ 2 mcg/mL) and the β-lactamase–producing organisms listed above.

To reduce the development of drug-resistant bacteria and maintain the effectiveness of Amoxicillin and Clavulanate Potassium 600 mg/42.9 mg per 5 mL and other antibacterial drugs, Amoxicillin and Clavulanate Potassium 600 mg/42.9 mg per 5 mL should be used only to treat or prevent infections that are proven or strongly suspected to be caused by susceptible bacteria. When culture and susceptibility information are available, they should be considered in selecting or modifying antibacterial therapy. In the absence of such data, local epidemiology and susceptibility patterns may contribute to the empiric selection of therapy.

CONTRAINDICATIONS

Amoxicillin and Clavulanate Potassium 600 mg/42.9 mg per 5 mL is contraindicated in patients with a history of allergic reactions to any penicillin. It is also contraindicated in patients with a previous history of cholestatic jaundice/hepatic dysfunction associated with AMOXICILLIN AND CLAVULANATE POTASSIUM.

WARNINGS

SERIOUS AND OCCASIONALLY FATAL HYPERSENSITIVITY (ANAPHYLACTIC) REACTIONS HAVE BEEN REPORTED IN PATIENTS ON PENICILLIN THERAPY. THESE REACTIONS ARE MORE LIKELY TO OCCUR IN INDIVIDUALS WITH A HISTORY OF PENICILLIN HYPERSENSITIVITY AND/OR A HISTORY OF SENSITIVITY TO MULTIPLE ALLERGENS. THERE HAVE BEEN REPORTS OF INDIVIDUALS WITH A HISTORY OF PENICILLIN HYPERSENSITIVITY WHO HAVE EXPERIENCED SEVERE REACTIONS WHEN TREATED WITH CEPHALOSPORINS. BEFORE INITIATING THERAPY WITH AMOXICILLIN AND CLAVULANATE POTASSIUM 600 MG/42.9 MG PER 5 ML, CAREFUL INQUIRY SHOULD BE MADE CONCERNING PREVIOUS HYPERSENSITIVITY REACTIONS TO PENICILLINS, CEPHALOSPORINS, OR OTHER ALLERGENS. IF AN ALLERGIC REACTION OCCURS, AMOXICILLIN AND CLAVULANATE POTASSIUM 600 MG/42.9 MG PER 5 ML SHOULD BE DISCONTINUED AND THE APPROPRIATE THERAPY INSTITUTED. SERIOUS ANAPHYLACTIC REACTIONS REQUIRE IMMEDIATE EMERGENCY TREATMENT WITH EPINEPHRINE. OXYGEN, INTRAVENOUS STEROIDS, AND AIRWAY MANAGEMENT, INCLUDING INTUBATION, SHOULD ALSO BE ADMINISTERED AS INDICATED.

Pseudomembranous colitis has been reported with nearly all antibacterial agents, including amoxicillin/clavulanate potassium, and has ranged in severity from mild to life-threatening. Therefore, it is important to consider this diagnosis in patients who present with diarrhea subsequent to the administration of antibacterial agents.

Treatment with antibacterial agents alters the normal flora of the colon and may permit overgrowth of clostridia. Studies indicate that a toxin produced by Clostridium difficile is one primary cause of “antibiotic-associated colitis.”

After the diagnosis of pseudomembranous colitis has been established, appropriate therapeutic measures should be initiated. Mild cases of pseudomembranous colitis usually respond to drug discontinuation alone. In moderate to severe cases, consideration should be given to management with fluids and electrolytes, protein supplementation, and treatment with an antibacterial drug clinically effective against C. difficile colitis.

Amoxicillin and Clavulanate Potassium 600 mg/42.9 mg per 5 mL should be used with caution in patients with evidence of hepatic dysfunction. Hepatic toxicity associated with the use of amoxicillin/clavulanate potassium is usually reversible. On rare occasions, deaths have been reported (less than 1 death reported per estimated 4 million prescriptions worldwide). These have generally been cases associated with serious underlying diseases or concomitant medications. (See CONTRAINDICATIONS and ADVERSE REACTIONS—Liver.)

PRECAUTIONS

General:

While amoxicillin/clavulanate possesses the characteristic low toxicity of the penicillin group of antibiotics, periodic assessment of organ system functions, including renal, hepatic, and hematopoietic function, is advisable if therapy is for longer than the drug is approved for administration.

A high percentage of patients with mononucleosis who receive ampicillin develop an erythematous skin rash. Thus, ampicillin-class antibiotics should not be administered to patients with mononucleosis.

The possibility of superinfections with mycotic or bacterial pathogens should be kept in mind during therapy. If superinfections occur (usually involving Pseudomonas or Candida), the drug should be discontinued and/or appropriate therapy instituted.

Prescribing Amoxicillin and Clavulanate Potassium 600 mg/42.9 mg per 5 mL in the absence of a proven or strongly suspected bacterial infection or a prophylactic indication is unlikely to provide benefit to the patient and increases the risk of the development of drug-resistant bacteria.

Information for the Patient:

Amoxicillin and Clavulanate Potassium 600 mg/42.9 mg per 5 mL should be taken every 12 hours with a meal or snack to reduce the possibility of gastrointestinal upset. If diarrhea develops and is severe or lasts more than 2 or 3 days, call your doctor.

Diarrhea is a common problem caused by antibiotics which usually ends when the antibiotic is discontinued. Sometimes after starting treatment with antibiotics, patients can develop watery and bloody stools (with or without stomach cramps and fever) even as late as 2 or more months after having taken the last dose of the antibiotic. If this occurs, patients should contact their physician as soon as possible.

Keep suspension refrigerated. Shake well before using. When dosing a child with the suspension (liquid) of Amoxicillin and Clavulanate Potassium 600 mg/42.9 mg per 5 mL, use a dosing spoon or medicine dropper. Be sure to rinse the spoon or dropper after each use. Bottles of suspension of Amoxicillin and Clavulanate Potassium 600 mg/42.9 mg per 5 mL may contain more liquid than required. Follow your doctor’s instructions about the amount to use and the days of treatment your child requires. Discard any unused medicine.

Patients should be counseled that antibacterial drugs, including Amoxicillin and Clavulanate Potassium 600 mg/42.9 mg per 5 mL, should only be used to treat bacterial infections. They do not treat viral infections (e.g., the common cold). When Amoxicillin and Clavulanate Potassium 600 mg/42.9 mg per 5 mL is prescribed to treat a bacterial infection, patients should be told that although it is common to feel better early in the course of therapy, the medication should be taken exactly as directed. Skipping doses or not completing the full course of therapy may: (1) decrease the effectiveness of the immediate treatment, and (2) increase the likelihood that bacteria will develop resistance and will not be treatable by Amoxicillin and Clavulanate Potassium 600 mg/42.9 mg per 5 mL or other antibacterial drugs in the future.

Phenylketonurics:

Each 5 mL of the 600 mg/42.9 mg per 5 mL suspension of Amoxicillin and Clavulanate Potassium contains 7 mg phenylalanine.

Drug Interactions:

Probenecid decreases the renal tubular secretion of amoxicillin. Concurrent use with Amoxicillin and Clavulanate Potassium 600 mg/42.9 mg per 5 mL may result in increased and prolonged blood levels of amoxicillin. Co-administration of probenecid cannot be recommended.

Abnormal prolongation of prothrombin time (increased international normalized ratio [INR]) has been reported rarely in patients receiving amoxicillin and oral anticoagulants. Appropriate monitoring should be undertaken when anticoagulants are prescribed concurrently. Adjustments in the dose of oral anticoagulants may be necessary to maintain the desired level of anticoagulation.

The concurrent administration of allopurinol and ampicillin increases substantially the incidence of rashes in patients receiving both drugs as compared to patients receiving ampicillin alone. It is not known whether this potentiation of ampicillin rashes is due to allopurinol or the hyperuricemia present in these patients. There are no data with Amoxicillin and Clavulanate Potassium 600 mg/42.9 mg per 5 mL and allopurinol administered concurrently.

In common with other broad-spectrum antibiotics, amoxicillin/clavulanate may reduce the efficacy of oral contraceptives.

Drug/Laboratory Test Interactions:

Oral administration of AMOXICILLIN AND CLAVULANATE POTASSIUM will result in high urine concentrations of amoxicillin. High urine concentrations of ampicillin may result in false-positive reactions when testing for the presence of glucose in urine using CLINITEST®, Benedict’s Solution, or Fehling’s Solution. Since this effect may also occur with amoxicillin and therefore Amoxicillin and Clavulanate Potassium 600 mg/42.9 mg per 5 mL, it is recommended that glucose tests based on enzymatic glucose oxidase reactions (such as CLINISTIX®) be used.

Following administration of ampicillin to pregnant women, a transient decrease in plasma concentration of total conjugated estriol, estriol-glucuronide, conjugated estrone, and estradiol has been noted. This effect may also occur with amoxicillin and therefore Amoxicillin and Clavulanate Potassium 600 mg/42.9 mg per 5 mL.

Carcinogenesis, Mutagenesis, Impairment of Fertility:

Long-term studies in animals have not been performed to evaluate carcinogenic potential. The mutagenic potential of AMOXICILLIN AND CLAVULANATE POTASSIUM was investigated in vitro with an Ames test, a human lymphocyte cytogenetic assay, a yeast test, and a mouse lymphoma forward mutation assay, and in vivo with mouse micronucleus tests and a dominant lethal test. All were negative apart from the in vitro mouse lymphoma assay where weak activity was found at very high, cytotoxic concentrations. AMOXICILLIN AND CLAVULANATE POTASSIUM at oral doses of up to 1,200 mg/kg/day (5.7 times the maximum adult human dose based on body surface area) was found to have no effect on fertility and reproductive performance in rats, dosed with a 2:1 ratio formulation of amoxicillin:clavulanate.

Teratogenic Effects:

Pregnancy (Category B). Reproduction studies performed in pregnant rats and mice given AMOXICILLIN AND CLAVULANATE POTASSIUM at oral dosages up to 1,200 mg/kg/day (4.9 and 2.8 times the maximum adult human oral dose based on body surface area, respectively), revealed no evidence of harm to the fetus due to AMOXICILLIN AND CLAVULANATE POTASSIUM. There are, however, no adequate and well-controlled studies in pregnant women. Because animal reproduction studies are not always predictive of human response, this drug should be used during pregnancy only if clearly needed.

Labor and Delivery:

Oral ampicillin-class antibiotics are generally poorly absorbed during labor. Studies in guinea pigs have shown that intravenous administration of ampicillin decreased the uterine tone, frequency of contractions, height of contractions, and duration of contractions. However, it is not known whether the use of AMOXICILLIN AND CLAVULANATE POTASSIUM in humans during labor or delivery has immediate or delayed adverse effects on the fetus, prolongs the duration of labor, or increases the likelihood that forceps delivery or other obstetrical intervention or resuscitation of the newborn will be necessary. In a single study in women with premature rupture of fetal membranes, it was reported that prophylactic treatment with AMOXICILLIN AND CLAVULANATE POTASSIUM may be associated with an increased risk of necrotizing enterocolitis in neonates.

Nursing Mothers:

Ampicillin-class antibiotics are excreted in human milk; therefore, caution should be exercised when AMOXICILLIN AND CLAVULANATE POTASSIUM is administered to a nursing woman.

Pediatric Use:

Safety and efficacy of Amoxicillin and Clavulanate Potassium 600 mg/42.9 mg per 5 mL in infants younger than 3 months have not been established. Safety and efficacy of Amoxicillin and Clavulanate Potassium 600 mg/42.9 mg per 5 mL have been demonstrated for treatment of acute otitis media in infants and children 3 months to 12 years (see Description of Clinical Studies).

The safety and effectiveness of Amoxicillin and Clavulanate Potassium 600 mg/42.9 mg per 5 mL have been established for the treatment of pediatric patients (3 months to 12 years) with acute bacterial sinusitis. This use is supported by evidence from adequate and well-controlled studies of AMOXICILLIN AND CLAVULANATE POTASSIUM Extended Release Tablets in adults with acute bacterial sinusitis, studies of Amoxicillin and Clavulanate Potassium 600 mg/42.9 mg per 5 mL in pediatric patients with acute otitis media, and by similar pharmacokinetics of amoxicillin and clavulanate in pediatric patients taking Amoxicillin and Clavulanate Potassium 600 mg/42.9 mg per 5 mL (see CLINICAL PHARMACOLOGY) and adults taking AMOXICILLIN AND CLAVULANATE POTASSIUM Extended Release Tablets.

ADVERSE REACTIONS

Amoxicillin and Clavulanate Potassium 600 mg/42.9 mg per 5 mL is generally well tolerated. The majority of side effects observed in pediatric clinical trials of acute otitis media were either mild or moderate, and transient in nature; 4.4% of patients discontinued therapy because of drug-related side effects. The most commonly reported side effects with probable or suspected relationship to Amoxicillin and Clavulanate Potassium 600 mg/42.9 mg per 5 mL were contact dermatitis, i.e., diaper rash (3.5%), diarrhea (2.9%), vomiting (2.2%), moniliasis (1.4%), and rash (1.1%). The most common adverse experiences leading to withdrawal that were of probable or suspected relationship to Amoxicillin and Clavulanate Potassium 600 mg/42.9 mg per 5 mL were diarrhea (2.5%) and vomiting (1.4%).

The following adverse reactions have been reported for ampicillin-class antibiotics:

Gastrointestinal:

Diarrhea, nausea, vomiting, indigestion, gastritis, stomatitis, glossitis, black “hairy” tongue, mucocutaneous candidiasis, enterocolitis, and hemorrhagic/pseudomembranous colitis. Onset of pseudomembranous colitis symptoms may occur during or after antibiotic treatment. (See WARNINGS.)

Hypersensitivity Reactions:

Skin rashes, pruritus, urticaria, angioedema, serum sickness−like reactions (urticaria or skin rash accompanied by arthritis, arthralgia, myalgia, and frequently fever), erythema multiforme (rarely Stevens-Johnson syndrome), acute generalized exanthematous pustulosis, and an occasional case of exfoliative dermatitis (including toxic epidermal necrolysis) have been reported. These reactions may be controlled with antihistamines and, if necessary, systemic corticosteroids. Whenever such reactions occur, the drug should be discontinued, unless the opinion of the physician dictates otherwise. Serious and occasional fatal hypersensitivity (anaphylactic) reactions can occur with oral penicillin. (See WARNINGS.)

Liver:

A moderate rise in AST (SGOT) and/or ALT (SGPT) has been noted in patients treated with ampicillin-class antibiotics, but the significance of these findings is unknown. Hepatic dysfunction, including increases in serum transaminases (AST and/or ALT), serum bilirubin, and/or alkaline phosphatase, has been infrequently reported with AMOXICILLIN AND CLAVULANATE POTASSIUM. It has been reported more commonly in the elderly, in males, or in patients on prolonged treatment. The histologic findings on liver biopsy have consisted of predominantly cholestatic, hepatocellular, or mixed cholestatic-hepatocellular changes. The onset of signs/symptoms of hepatic dysfunction may occur during or several weeks after therapy has been discontinued. The hepatic dysfunction, which may be severe, is usually reversible. On rare occasions, deaths have been reported (less than 1 death reported per estimated 4 million prescriptions worldwide). These have generally been cases associated with serious underlying diseases or concomitant medications.

Renal:

Interstitial nephritis and hematuria have been reported rarely. Crystalluria has also been reported (see OVERDOSAGE).

Hemic and Lymphatic Systems:

Anemia, including hemolytic anemia, thrombocytopenia, thrombocytopenic purpura, eosinophilia, leukopenia, and agranulocytosis have been reported during therapy with penicillins. These reactions are usually reversible on discontinuation of therapy and are believed to be hypersensitivity phenomena. A slight thrombocytosis was noted in less than 1% of the patients treated with AMOXICILLIN AND CLAVULANATE POTASSIUM. There have been reports of increased prothrombin time in patients receiving AMOXICILLIN AND CLAVULANATE POTASSIUM and anticoagulant therapy concomitantly.

Central Nervous System:

Agitation, anxiety, behavioral changes, confusion, convulsions, dizziness, insomnia, and reversible hyperactivity have been reported rarely.

Miscellaneous:

Tooth discoloration (brown, yellow, or gray staining) has been rarely reported. Most reports occurred in pediatric patients. Discoloration was reduced or eliminated with brushing or dental cleaning in most cases.

OVERDOSAGE

Following overdosage, patients have experienced primarily gastrointestinal symptoms including stomach and abdominal pain, vomiting, and diarrhea. Rash, hyperactivity, or drowsiness have also been observed in a small number of patients.

In the case of overdosage, discontinue Amoxicillin and Clavulanate Potassium 600 mg/42.9 mg per 5 mL, treat symptomatically, and institute supportive measures as required. If the overdosage is very recent and there is no contraindication, an attempt at emesis or other means of removal of drug from the stomach may be performed. A prospective study of 51 pediatric patients at a poison control center suggested that overdosages of less than 250 mg/kg of amoxicillin are not associated with significant clinical symptoms and do not require gastric emptying.^4

Interstitial nephritis resulting in oliguric renal failure has been reported in a small number of patients after overdosage with amoxicillin.

Crystalluria, in some cases leading to renal failure, has also been reported after amoxicillin overdosage in adult and pediatric patients. In case of overdosage, adequate fluid intake and diuresis should be maintained to reduce the risk of amoxicillin crystalluria.

Renal impairment appears to be reversible with cessation of drug administration. High blood levels may occur more readily in patients with impaired renal function because of decreased renal clearance of both amoxicillin and clavulanate. Both amoxicillin and clavulanate are removed from the circulation by hemodialysis.

DOSAGE AND ADMINISTRATION

Amoxicillin and Clavulanate Potassium, 600 mg/42.9 mg per 5 mL, does not contain the same amount of clavulanic acid (as the potassium salt) as any of the other suspensions of AMOXICILLIN AND CLAVULANATE POTASSIUM. Amoxicillin and Clavulanate Potassium 600 mg/42.9 mg per 5 mL contains 42.9 mg of clavulanic acid per 5 mL, whereas the 200 mg/5 mL suspension of AMOXICILLIN AND CLAVULANATE POTASSIUM contains 28.5 mg of clavulanic acid per 5 mL and the 400 mg/5 mL suspension contains 57 mg of clavulanic acid per 5 mL. Therefore, the 200 mg/28.5 mg/5 mL and 400 mg/57 mg/5 mL suspensions of AMOXICILLIN AND CLAVULANATE POTASSIUM should not be substituted for Amoxicillin and Clavulanate Potassium 600 mg/42.9 mg per 5 mL as they are not interchangeable.

Dosage:

Pediatric patients 3 months and older:

Based on the amoxicillin component (600 mg/5 mL), the recommended dose of Amoxicillin and Clavulanate Potassium 600 mg/42.9 mg per 5 mL is 90 mg/kg/day divided every 12 hours, administered for 10 days (see chart below).

Body Weight (kg) | Volume of Amoxicillin and Clavulanate Potassium 600 mg/42.9 mg per 5 mL providing 90 mg/kg/day
8 | 3.0 mL twice daily
12 | 4.5 mL twice daily
16 | 6.0 mL twice daily
20 | 7.5 mL twice daily
24 | 9.0 mL twice daily
28 | 10.5 mL twice daily
32 | 12.0 mL twice daily
36 | 13.5 mL twice daily

Pediatric patients weighing 40 kg and more:

Experience with Amoxicillin and Clavulanate Potassium (600 mg/5 mL formulation) in this group is not available.

Adults:

Experience with Amoxicillin and Clavulanate Potassium (600 mg/5 mL formulation) in adults is not available and adults who have difficulty swallowing should not be given Amoxicillin and Clavulanate Potassium (600 mg/5 mL) in place of the 500-mg or 875-mg tablet of AMOXICILLIN AND CLAVULANATE POTASSIUM.

Hepatically impaired patients should be dosed with caution and hepatic function monitored at regular intervals. (See WARNINGS.)

Directions for Mixing Oral Suspension:

Prepare a suspension at time of dispensing as follows: Tap bottle until all the powder flows freely. Add approximately 2/3 of the total amount of water for reconstitution (see table below) and shake vigorously to suspend powder. Add remainder of the water and again shake vigorously.

Amoxicillin and Clavulanate Potassium (600 mg/5 mL Suspension)
Bottle Size | Amount of Water Required for Reconstitution
75 mL | 70 mL
125 mL | 110 mL
200 mL | 180 mL

Each teaspoonful (5 mL) will contain 600 mg amoxicillin as the trihydrate and 42.9 mg of clavulanic acid as the potassium salt.

NOTE: SHAKE ORAL SUSPENSION WELL BEFORE USING.

Information for the Pharmacist:

For patients who wish to alter the taste of Amoxicillin and Clavulanate Potassium 600 mg/42.9 mg per 5 mL, immediately after reconstitution 1 drop of FLAVORx™ (apple, banana cream, bubble gum, cherry, or watermelon flavor) may be added for every 5 mL of Amoxicillin and Clavulanate Potassium 600 mg/42.9 mg per 5 mL. The resulting suspension is stable for 10 days under refrigeration. Stability of Amoxicillin and Clavulanate Potassium 600 mg/42.9 mg per 5 mL when mixed with other flavors distributed by FLAVORx has not been evaluated for flavors other than the 5 flavors listed above.

Administration:

To minimize the potential for gastrointestinal intolerance, Amoxicillin and Clavulanate Potassium 600 mg/42.9 mg per 5 mL should be taken at the start of a meal. Absorption of clavulanate potassium may be enhanced when Amoxicillin and Clavulanate Potassium 600 mg/42.9 mg per 5 mL is administered at the start of a meal.

HOW SUPPLIED

Amoxicillin and Clavulanate Potassium, 600 mg/5 mL, for Oral Suspension: Each 5 mL of reconstituted strawberry cream-flavored suspension contains 600 mg amoxicillin and 42.9 mg clavulanic acid as the potassium salt.

HOW SUPPLIED

NDC 43598-203-51 75 mL bottle

NDC 43598-203-69 125 mL bottle

NDC 43598-203-54 200 mL bottle

STORAGE

Store reconstituted suspension under refrigeration. Discard unused suspension after 10 days. Store dry powder for oral suspension at or below 25°C (77°F). Dispense in original container.

Description of Clinical Studies

Two clinical studies were conducted in pediatric patients with acute otitis media.

A non-comparative, open-label study assessed the bacteriologic and clinical efficacy of Amoxicillin and Clavulanate Potassium 600 mg/42.9 mg per 5 mL (90/6.4 mg/kg/day, divided every 12 hours) for 10 days in 521 pediatric patients (3 to 50 months) with acute otitis media. The primary objective was to assess bacteriological response in children with acute otitis media due to S. pneumoniae with amoxicillin/clavulanic acid MICs of 4 mcg/mL. The study sought the enrollment of patients with the following risk factors: Failure of antibiotic therapy for acute otitis media in the previous 3 months, history of recurrent episodes of acute otitis media, ≤ 2 years, or daycare attendance. Prior to receiving Amoxicillin and Clavulanate Potassium 600 mg/42.9 mg per 5 mL, all patients had tympanocentesis to obtain middle ear fluid for bacteriological evaluation. Patients from whom S. pneumoniae (alone or in combination with other bacteria) was isolated had a second tympanocentesis 4 to 6 days after the start of therapy. Clinical assessments were planned for all patients during treatment (4-6 days after starting therapy), as well as 2-4 days post-treatment and 15-18 days post-treatment. Bacteriological success was defined as the absence of the pretreatment pathogen from the on-therapy tympanocentesis specimen. Clinical success was defined as improvement or resolution of signs and symptoms. Clinical failure was defined as lack of improvement or worsening of signs and/or symptoms at any time following at least 72 hours of Amoxicillin and Clavulanate Potassium 600 mg/42.9 mg per 5 mL; patients who received an additional systemic antibacterial drug for otitis media after 3 days of therapy were considered clinical failures. Bacteriological eradication on therapy (day 4-6 visit) in the per protocol population is summarized in the following table:

Table 5. Bacteriologic Eradication Rates in the Per Protocol Population
 | Bacteriologic Eradication on Therapy
Pathogen | n/N | % | 95% CI [CI = confidence intervals; 95% CIs are not adjusted for multiple comparisons.]
All S. pneumoniae | 121/123 | 98.4 | (94.3, 99.8)
S. pneumoniae with penicillin MIC = 2 mcg/mL | 19/19 | 100 | (82.4, 100.0)
S. pneumoniae with penicillin MIC = 4 mcg/mL | 12/14 | 85.7 | (57.2, 98.2)
H. influenzae | 75/81 | 92.6 | (84.6, 97.2)
M. catarrhalis | 11/11 | 100 | (71.5, 100.0)

Clinical assessments were made in the per protocol population 2-4 days post-therapy and 15-18 days post-therapy. Patients who responded to therapy 2-4 days post-therapy were followed for 15-18 days post-therapy to assess them for acute otitis media. Nonresponders at 2-4 days post-therapy were considered failures at the latter timepoint.

Table 6. Clinical Assessments in the Per Protocol Population (Includes S. pneumoniae Patients With Penicillin MICs = 2 or 4 mcg/mL [S. pneumoniae strains with penicillin MICs of 2 or 4 mcg/mL are considered resistant to penicillin.])
 | 2-4 Days Post-Therapy (Primary Endpoint)
Pathogen | n/N | % | 95% CI [CI = confidence intervals; 95% CIs are not adjusted for multiple comparisons.]
All S. pneumoniae | 122/137 | 89.1 | (82.6, 93.7)
S. pneumoniae with penicillin MIC = 2 mcg/mL | 17/20 | 85.0 | (62.1, 96.8)
S. pneumoniae with penicillin MIC = 4 mcg/mL | 11/14 | 78.6 | (49.2, 95.3)
H. influenzae | 141/162 | 87.0 | (80.9, 91.8)
M. catarrhalis | 22/26 | 84.6 | (65.1, 95.6)
 | 15-18 Days Post-Therapy [Clinical assessments at 15-18 days post-therapy may have been confounded by viral infections and new episodes of acute otitis media with time elapsed post-treatment.] (Secondary Endpoint)
Pathogen | n/N | % | 95% CI
All S. pneumoniae | 95/136 | 69.9 | (61.4, 77.4)
S. pneumoniae with penicillin MIC = 2 mcg/mL | 11/20 | 55.0 | (31.5, 76.9)
S. pneumoniae with penicillin MIC = 4 mcg/mL | 5/14 | 35.7 | (12.8, 64.9)
H. influenzae | 106/156 | 67.9 | (60.0, 75.2)
M. catarrhalis | 14/25 | 56.0 | (34.9, 75.6)

In the intent-to-treat analysis, overall clinical outcomes at 2-4 days and 15-18 days post-treatment in patients with S. pneumoniae with penicillin MIC = 2 mcg/mL and 4 mcg/mL were 29/41 (71%) and 17/41 (41.5%), respectively.

In the intent-to-treat population of 521 patients, the most frequently reported adverse events were vomiting (6.9%), fever (6.1%), contact dermatitis (i.e., diaper rash) (6.1%), upper respiratory tract infection (4.0%), and diarrhea (3.8%). Protocol-defined diarrhea (i.e., 3 or more watery stools in one day or 2 watery stools per day for 2 consecutive days as recorded on diary cards) occurred in 12.9% of patients.

A double-blind, randomized, clinical study compared Amoxicillin and Clavulanate Potassium 600 mg/42.9 mg per 5 mL (90/6.4 mg/kg/day, divided every 12 hours) to AMOXICILLIN AND CLAVULANATE POTASSIUM (45/6.4 mg/kg/day, divided every 12 hours) for 10 days in 450 pediatric patients (3 months to 12 years) with acute otitis media. The primary objective of the study was to compare the safety of Amoxicillin and Clavulanate Potassium 600 mg/42.9 mg per 5 mL to AMOXICILLIN AND CLAVULANATE POTASSIUM. There was no statistically significant difference between treatments in the proportion of patients with 1 or more adverse events. The most frequently reported adverse events for Amoxicillin and Clavulanate Potassium 600 mg/42.9 mg per 5 mL and the comparator of AMOXICILLIN AND CLAVULANATE POTASSIUM were coughing (11.9% versus 6.8%), vomiting (6.5% versus 7.7%), contact dermatitis (i.e., diaper rash, 6.0% versus 4.8%), fever (5.5% versus 3.9%), and upper respiratory infection (3.0% versus 9.2%), respectively. The frequencies of protocol-defined diarrhea with Amoxicillin and Clavulanate Potassium 600 mg/42.9 mg per 5 mL(11.1%) and AMOXICILLIN AND CLAVULANATE POTASSIUM (9.4%) were similar (95% confidence interval on difference: –4.2% to 7.7%). Only 2 patients in the group treated with Amoxicillin and Clavulanate Potassium 600 mg/42.9 mg per 5mL and 1 patient in the group treated with AMOXICILLIN AND CLAVULANATE POTASSIUM were withdrawn due to diarrhea.

REFERENCES

1. Clinical and Laboratory Standards Institute (CLSI). Performance Standards for Antimicrobial Susceptibility Testing – 21st Informational Supplement. CSLI Document M100-S21. CLSI, 940 West Valley Rd., Suite 1400, Wayne, PA 19087, 2011.
2. Clinical and Laboratory Standards Institute (CLSI). Methods for Antimicrobial Susceptibility Testing of Anaerobic Bacteria – Approved Standard 7th ed. CSLI Document M11-A7. CLSI, 940 West Valley Rd., Suite 1400, Wayne, PA 19087, 2007.
3. Clinical and Laboratory Standards Institute (CLSI). Methods for Dilution Antimicrobial Susceptibility Tests for Bacteria That Grow Aerobically; Approved Standard – 8th ed. CLSI Document M07-A8. CLSI, 940 West Valley Rd., Suite 1400, Wayne, PA 19087, 2009.
4. Clinical and Laboratory Standards Institute (CLSI). Performance Standards for Antimicrobial Disk Susceptibility Test; Approved Standard – 10th ed. CLSI Document M02-A10. CLSI, 940 West Valley Rd., Suite 1400, Wayne, PA 19087, 2009.
5. Swanson-Biearman B, Dean BS, Lopez G, Krenzelok EP. The effects of penicillin and cephalosporin ingestions in children less than six years of age. Vet Hum Toxicol 1988;30:66-67.

CLINITEST is a registered trademark of Miles, Inc.

CLINISTIX is a registered trademark of Bayer Corporation.

FLAVORx is a trademark of FLAVORx. Inc.

Mfd. by:

Dr. Reddy's Laboratories Inc.,

Bridgewater, NJ 08807